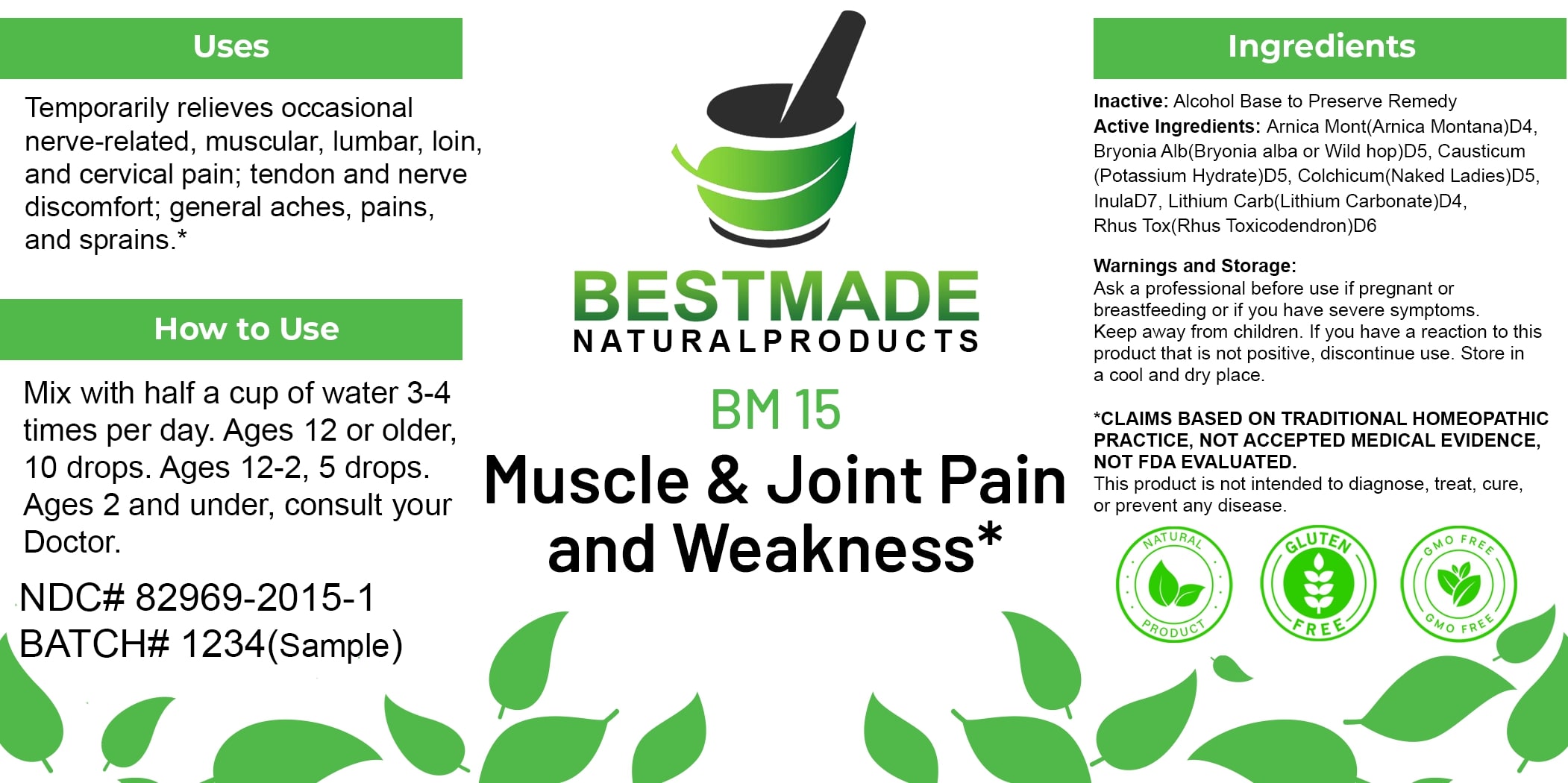 DRUG LABEL: Bestmade Natural Products BM15
NDC: 82969-2015 | Form: LIQUID
Manufacturer: Bestmade Natural Products
Category: homeopathic | Type: HUMAN OTC DRUG LABEL
Date: 20250122

ACTIVE INGREDIENTS: INULA HELENIUM ROOT 30 [hp_C]/30 [hp_C]; TOXICODENDRON PUBESCENS LEAF 30 [hp_C]/30 [hp_C]; COLCHICUM AUTUMNALE BULB 30 [hp_C]/30 [hp_C]; ARNICA MONTANA 30 [hp_C]/30 [hp_C]; BRYONIA ALBA ROOT 30 [hp_C]/30 [hp_C]; CAUSTICUM 30 [hp_C]/30 [hp_C]; LITHIUM CARBONATE 30 [hp_C]/30 [hp_C]
INACTIVE INGREDIENTS: ALCOHOL 30 [hp_C]/30 [hp_C]

BM15

DOSAGE AND ADMINISTRATION

How to Use

Mix with half a cup of water 3-4 times per day. Ages 12 or older, 10 drops. Ages 12-2, 5 drops. Ages 2 and under, consult your Doctor.

INACTIVE INGREDIENT

Ingredients

Inactive: Alcohol Base to Preserve Remedy

Uses

Temporarily relieves occasional nerve-related, muscular, lumbar, loin, and cervical pain; tendon and nerve discomfort; general aches, pains, and sprains.*

*CLAIMS BASED ON TRADITIONAL HOMEOPATHIC PRACTICE, NOT ACCEPTED MEDICAL EVIDENCE, NOT FDA EVALUATED.
This product is not intended to diagnose, treat, cure, or prevent any disease.

Active Ingredients:

Arnica Mont(Arnica Montana)D4, Bryonia Alb(Bryonia alba or Wild hop)D5, Causticum (Potassium Hydrate)D5, Colchicum(Naked Ladies)D5, InulaD7, Lithium Carb(Lithium Carbonate)D4, Rhus Tox(Rhus Toxicodendron)D6

KEEP OUT OF REACH OF CHILDREN

Warnings and Storage:

Ask a professional before use if pregnant or breastfeeding or if you have severe symptoms. Keep away from children. If you have a reaction to this product this is not positive, discontinue use. Store in a cool and dry place.

Warnings and Storage:

Ask a professional before use if pregnant or breastfeeding or if you have severe symptoms. Keep away from children. If you have a reaction to this product this is not positive, discontinue use. Store in a cool and dry place.

*CLAIMS BASED ON TRADITIONAL HOMEOPATHIC PRACTICE, NOT ACCEPTED MEDICAL EVIDENCE, NOT FDA EVALUATED.
This product is not intended to diagnose, treat, cure, or prevent any disease.

Uses

Temporarily relieves occasional nerve-related, muscular, lumbar, loin, and cervical pain; tendon and nerve discomfort; general aches, pains, and sprains.*

*CLAIMS BASED ON TRADITIONAL HOMEOPATHIC PRACTICE, NOT ACCEPTED MEDICAL EVIDENCE, NOT FDA EVALUATED.
This product is not intended to diagnose, treat, cure, or prevent any disease.

Entire package label